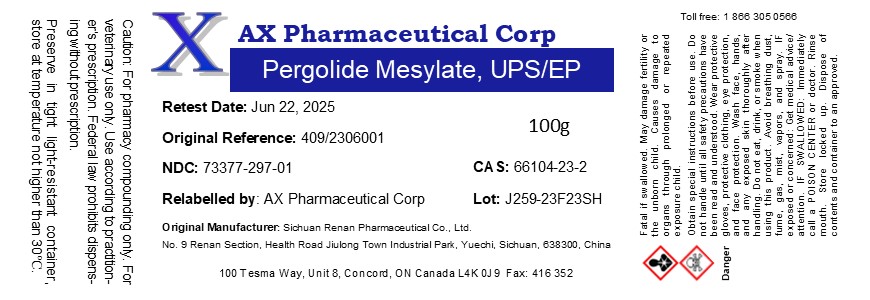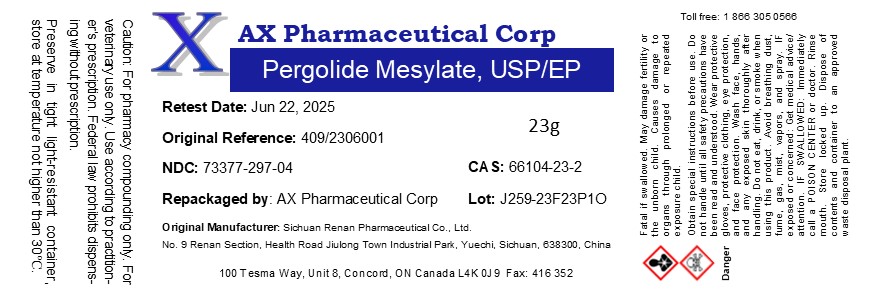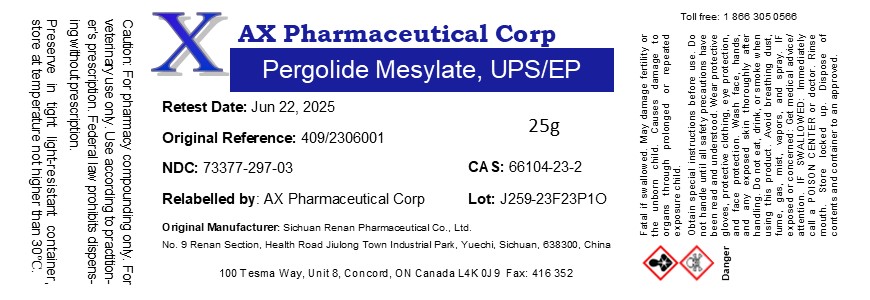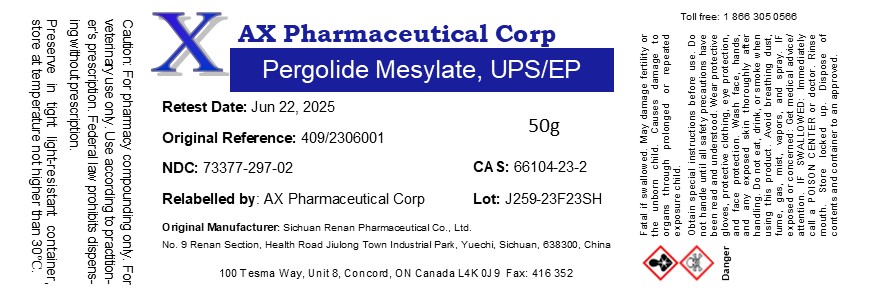 DRUG LABEL: Pergolide Mesylate
NDC: 73377-297 | Form: POWDER
Manufacturer: AX Pharmaceutical Corp
Category: other | Type: BULK INGREDIENT - ANIMAL DRUG
Date: 20250304

ACTIVE INGREDIENTS: Pergolide Mesylate 1 g/1 g

Pergolide Mesylate